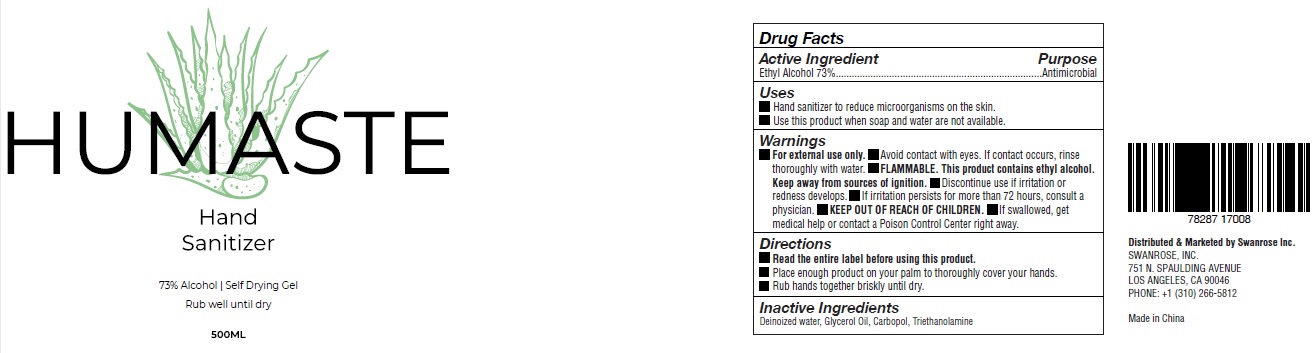 DRUG LABEL: HUMASTE Hand Sanitizer
NDC: 78287-170 | Form: GEL
Manufacturer: Swanrose, Inc.
Category: otc | Type: HUMAN OTC DRUG LABEL
Date: 20200629

ACTIVE INGREDIENTS: ALCOHOL 73 mL/100 mL
INACTIVE INGREDIENTS: WATER; GLYCERIN; CARBOMER HOMOPOLYMER, UNSPECIFIED TYPE; TROLAMINE

HUMASTE Hand Sanitizer

Active Ingredient

Ethyl Alcohol 73%

Purpose

Antimicrobial

Uses

• Hand sanitizer to reduce microorganisms on the skin.
• Use this product when soap and water are not available.

Warnings

• For external use only. • Avoid contact with eyes. If contact occurs, rinse thoroughly with water. • FLAMMABLE. This product contains ethyl alcohol. Keep away from sources of ignition. • Discontinue use if irritation or redness develops. • If irritation persists for more than 72 hours, consult a physician.

• KEEP OUT OF REACH OF CHILDREN.

• If swallowed, get medical help or contact a Poison Control Center right away.

Directions

• Read the entire label before using this product.
• Place enough product on your palm to thoroughly cover your hands.
• Rub hands together briskly until dry.

Inactive Ingredients

Deinoized water, Glycerol Oil, Carbopol, Triethanolamine

73% Alcohol | Self Drying Gel
Rub well until dry

Distributed & Marketed by Swanrose Inc.
SWANROSE, INC.
751 N. SPAULDING AVENUE
LOS ANGELES, CA 90046
PHONE: +1 (310) 266-5812
Made in China